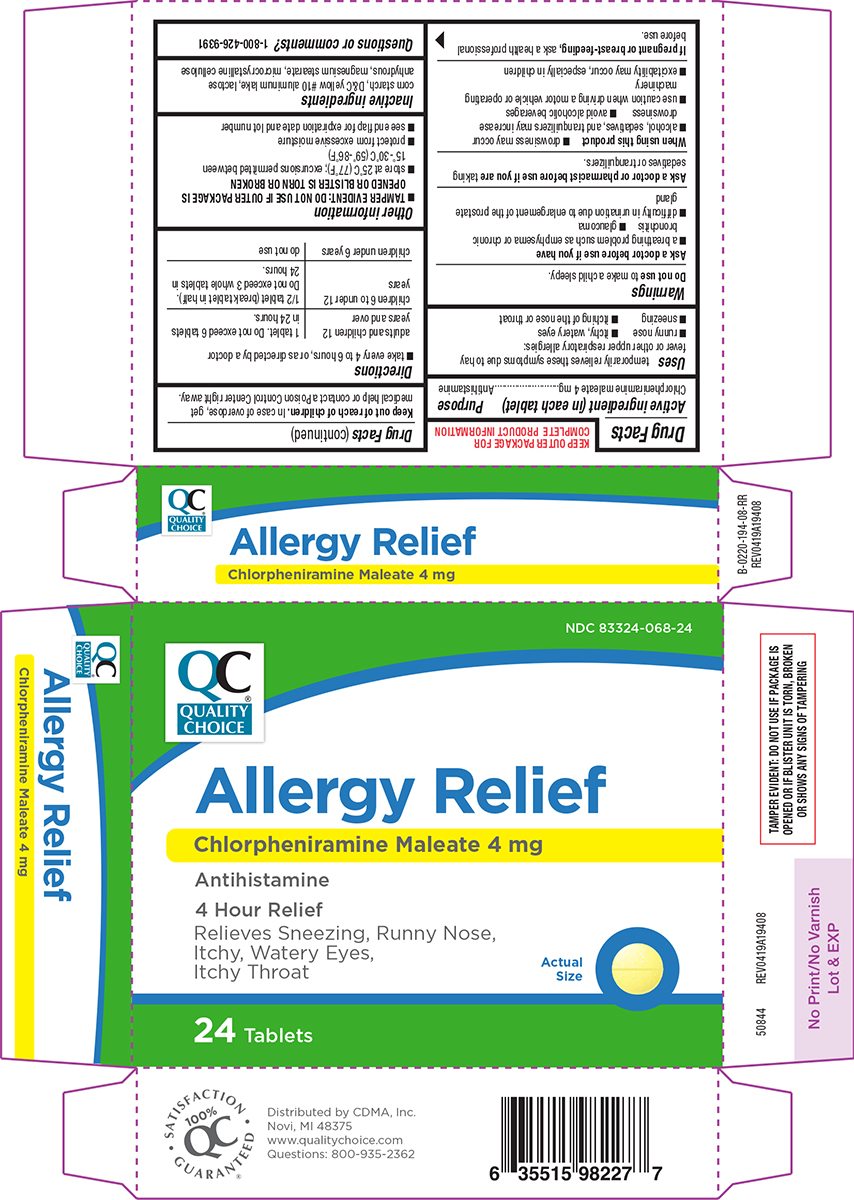 DRUG LABEL: Allergy Relief
NDC: 83324-068 | Form: TABLET
Manufacturer: Chain Drug Marketing Association, Inc.
Category: otc | Type: HUMAN OTC DRUG LABEL
Date: 20250904

ACTIVE INGREDIENTS: CHLORPHENIRAMINE MALEATE 4 mg/1 1
INACTIVE INGREDIENTS: STARCH, CORN; D&C YELLOW NO. 10 ALUMINUM LAKE; ANHYDROUS LACTOSE; MAGNESIUM STEARATE; MICROCRYSTALLINE CELLULOSE

Quality Choice 44-194

Active ingredient (in each tablet)

Chlorpheniramine maleate 4 mg

Purpose

Antihistamine

Uses

temporarily relieves these symptoms due to hay fever or other upper respiratory allergies:

- runny nose
- sneezing
- itchy, watery eyes
- itching of the nose or throat

Warnings

Do not use

to make a child sleepy.

Ask a doctor before use if you have

- a breathing problem such as emphysema or chronic bronchitis
- glaucoma
- difficulty in urination due to enlargement of the prostate gland

Ask a doctor or pharmacist before use if you are

taking sedatives or tranquilizers.

When using this product

- drowsiness may occur
- avoid alcoholic beverages
- alcohol, sedatives, and tranquilizers may increase drowsiness
- use caution when driving a motor vehicle or operating machinery
- excitability may occur, especially in children

If pregnant or breast-feeding,

ask a health professional before use.

Keep out of reach of children.

In case of overdose, get medical help or contact a Poison Control Center right away.

Directions

- take every 4 to 6 hours, or as directed by a doctor

adults and children 12 years and over | 1 tablet. Do not exceed 6 tablets in 24 hours.
children 6 to under 12 years | 1/2 tablet (break tablet in half). Do not exceed 3 whole tablets in 24 hours.
children under 6 years | do not use

Other information

- store at 25ºC (77ºF); excursions permitted between 15º-30ºC (59º-86ºF)
- protect from excessive moisture
- see end flap for expiration date and lot number

Inactive ingredients

corn starch, D&C yellow #10 aluminum lake, lactose anhydrous, magnesium stearate, microcrystalline cellulose

Questions or comments?

1-800-426-9391

Principal Display Panel

NDC 83324-068-24

QC®
QUALITY
CHOICE

Allergy Relief
Chlorpheniramine Maleate 4 mg
Antihistamine
4 Hour Relief
Relieves Sneezing, Runny Nose,
Itchy, Watery Eyes,
Itchy Throat

Actual
Size

24 Tablets

TAMPER EVIDENT: DO NOT USE IF PACKAGE IS
OPENED OR IF BLISTER UNIT IS TORN, BROKEN
OR SHOWS ANY SIGNS OF TAMPERING

• SATISFACTION
100%
QC®
GUARATNTEED •

Distributed by CDMA, Inc.
Novi, MI 48375
www.qualitychoice.com
Questions: 800-935-2362

50844 REV0419A19408

Quality Choice 44-194